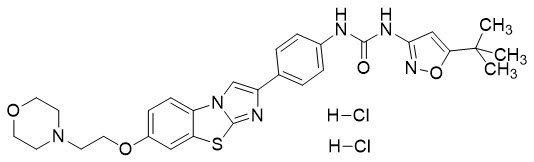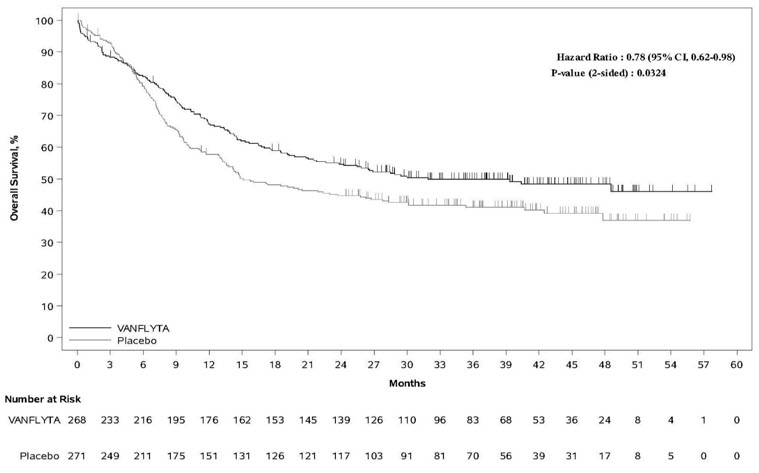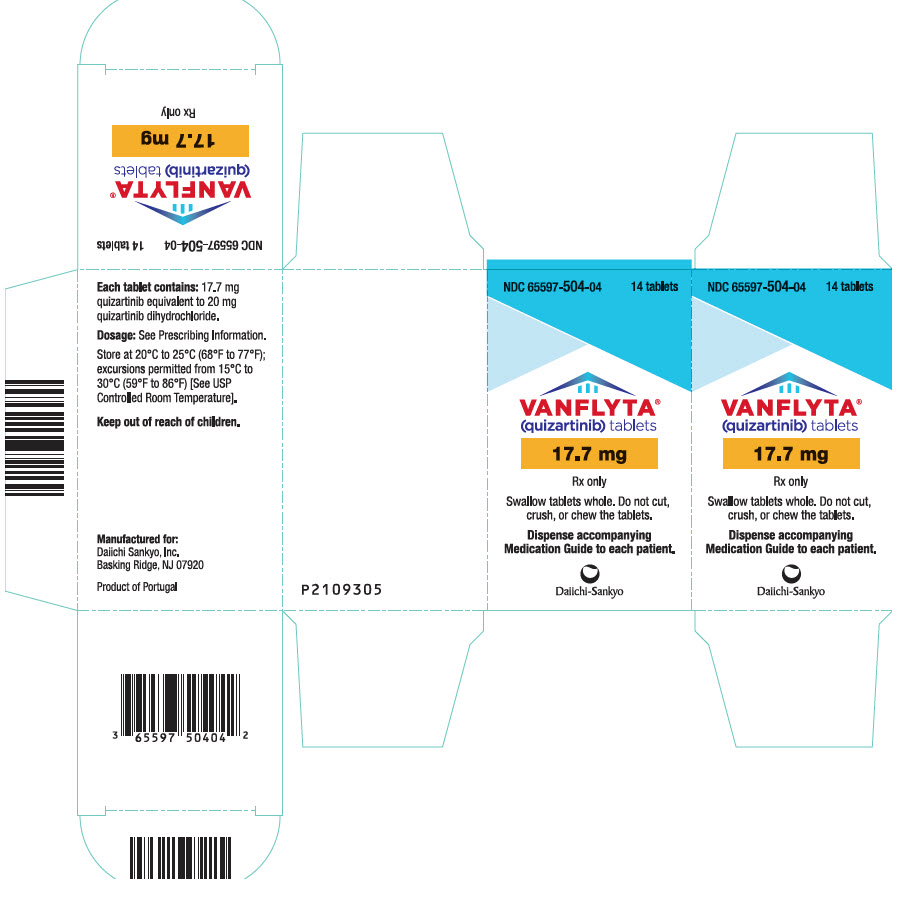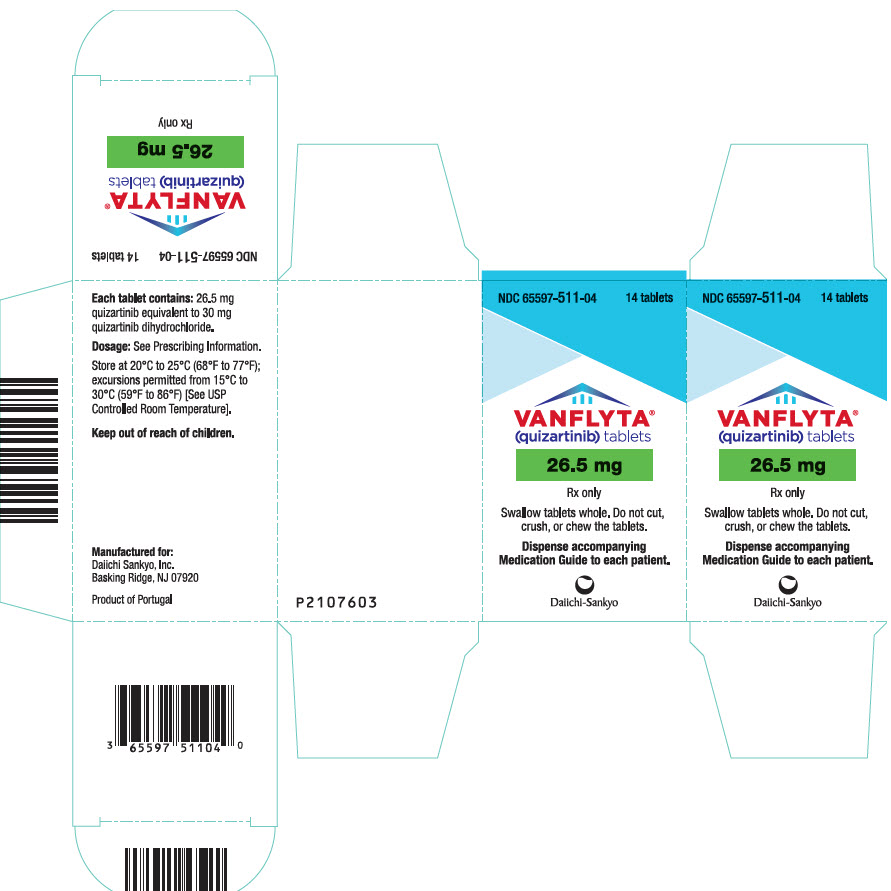 DRUG LABEL: VANFLYTA
NDC: 65597-504 | Form: TABLET, FILM COATED
Manufacturer: Daiichi Sankyo Inc.
Category: prescription | Type: HUMAN PRESCRIPTION DRUG LABEL
Date: 20251112

ACTIVE INGREDIENTS: QUIZARTINIB DIHYDROCHLORIDE 17.7 mg/1 1
INACTIVE INGREDIENTS: HYDROXYPROPYL BETADEX; MICROCRYSTALLINE CELLULOSE; HYPROMELLOSE, UNSPECIFIED; MAGNESIUM STEARATE; TALC; TRIACETIN; TITANIUM DIOXIDE

HIGHLIGHTS OF PRESCRIBING INFORMATION

These highlights do not include all the information needed to use VANFLYTA safely and effectively. See full prescribing information for VANFLYTA.
VANFLYTA® (quizartinib) tablets, for oral use
Initial U.S. Approval: 2023

WARNING: QT PROLONGATION, TORSADES DE POINTES, and CARDIAC ARREST

See full prescribing information for complete boxed warning.

- VANFLYTA prolongs the QT interval. (12.2) Prior to VANFLYTA administration and periodically, perform electrocardiograms (ECGs), monitor for hypokalemia or hypomagnesemia, and correct deficiencies. (2.3, 5.1)
- Torsades de pointes and cardiac arrest have occurred in patients receiving VANFLYTA. Do not administer VANFLYTA to patients with severe hypokalemia, severe hypomagnesemia, or long QT syndrome. (4, 5.1)
- Do not initiate treatment with VANFLYTA or escalate the VANFLYTA dose if the QT interval corrected by Fridericia's formula (QTcF) is greater than 450 ms. (2.3, 5.1)
- Monitor ECGs more frequently if concomitant use of drugs known to prolong the QT interval is required. (2.3, 5.1)
- Reduce the VANFLYTA dose when used concomitantly with strong CYP3A inhibitors, as they may increase quizartinib exposure. (2.4, 5.1)
- VANFLYTA is available only through a restricted program called the VANFLYTA Risk Evaluation and Mitigation Strategy (REMS). (5.2)

1 INDICATIONS AND USAGE

VANFLYTA is a kinase inhibitor indicated in combination with standard cytarabine and anthracycline induction and cytarabine consolidation, and as maintenance monotherapy following consolidation chemotherapy, for the treatment of adult patients with newly diagnosed acute myeloid leukemia (AML) that is FLT3 internal tandem duplication (ITD)-positive as detected by an FDA-approved test. (1)

Limitations of Use:

VANFLYTA is not indicated as maintenance monotherapy following allogeneic hematopoietic stem cell transplantation (HSCT); improvement in overall survival with VANFLYTA in this setting has not been demonstrated. (1)

2 DOSAGE AND ADMINISTRATION

- Take VANFLYTA tablets orally once daily with or without food at approximately the same time each day. (2.2)
- See Full Prescribing Information for recommended VANFLYTA dosage regimen and dosage modifications. (2.2, 2.3, 2.4)

3 DOSAGE FORMS AND STRENGTHS

Tablets: 17.7 mg or 26.5 mg. (3)

4 CONTRAINDICATIONS

Contraindicated in patients with severe hypokalemia, severe hypomagnesemia, long QT syndrome, or in patients with a history of ventricular arrhythmias or torsades de pointes. (4, 5.1)

5 WARNINGS AND PRECAUTIONS

- QT Prolongation, Torsades de Pointes, and Cardiac Arrest: Monitor electrocardiograms and levels of serum electrolytes. Reduce, interrupt, or permanently discontinue VANFLYTA as appropriate. (2.3, 5.1)
- Embryo-Fetal Toxicity: VANFLYTA can cause fetal harm. Advise females of reproductive potential and males with female partners of reproductive potential of potential risk to a fetus and to use effective contraception. (5.3, 8.1, 8.3)

6 ADVERSE REACTIONS

The most common (>20%) adverse reactions, including laboratory abnormalities, are lymphocytes decreased, potassium decreased, albumin decreased, phosphorus decreased, alkaline phosphatase increased, magnesium decreased, febrile neutropenia, diarrhea, mucositis, nausea, calcium decreased, abdominal pain, sepsis, neutropenia, headache, creatine phosphokinase increased, vomiting, and upper respiratory tract infection. (6.1)

To report SUSPECTED ADVERSE REACTIONS, contact Daiichi Sankyo, Inc. at 1-877-437-7763 or FDA at 1-800-FDA-1088 or www.fda.gov/medwatch.

7 DRUG INTERACTIONS

- Strong CYP3A Inhibitors: Reduce the VANFLYTA dose. (2.4, 7)
- Strong or Moderate CYP3A Inducers: Avoid concomitant use. (7, 12.3)

8 USE IN SPECIFIC POPULATIONS

Lactation: Advise not to breastfeed. (8.2)

FULL PRESCRIBING INFORMATION

WARNING: QT PROLONGATION, TORSADES DE POINTES, and CARDIAC ARREST

- VANFLYTA prolongs the QT interval in a dose- and concentration-related manner [see Clinical Pharmacology (12.2)]. Prior to VANFLYTA administration and periodically, monitor for hypokalemia or hypomagnesemia, and correct deficiencies. Perform ECGs to monitor the QTc at baseline, weekly during induction and consolidation therapy, weekly for at least the first month of maintenance, and periodically thereafter [see Dosage and Administration (2.3) and Warnings and Precautions (5.1)].
- Torsades de pointes and cardiac arrest have occurred in patients receiving VANFLYTA. Do not administer VANFLYTA to patients with severe hypokalemia, severe hypomagnesemia, or long QT syndrome [see Contraindications (4) and Warnings and Precautions (5.1)].
- Do not initiate treatment with VANFLYTA or escalate the VANFLYTA dose if the QT interval corrected by Fridericia's formula (QTcF) is greater than 450 ms [see Dosage and Administration (2.3) and Warnings and Precautions (5.1)].
- Monitor ECGs more frequently if concomitant use of drugs known to prolong the QT interval is required [see Dosage and Administration (2.3) and Warnings and Precautions (5.1)].
- Reduce the VANFLYTA dose when used concomitantly with strong CYP3A inhibitors, as they may increase quizartinib exposure [see Dosage and Administration (2.4) and Warnings and Precautions (5.1)].
- Because of the risk of QT prolongation, VANFLYTA is available only through a restricted program under a Risk Evaluation and Mitigation Strategy (REMS) called the VANFLYTA REMS [see Warnings and Precautions (5.2)].

1 INDICATIONS AND USAGE

VANFLYTA is indicated in combination with standard cytarabine and anthracycline induction and cytarabine consolidation, and as maintenance monotherapy following consolidation chemotherapy, for the treatment of adult patients with newly diagnosed acute myeloid leukemia (AML) that is FLT3 internal tandem duplication (ITD)-positive as detected by an FDA-approved test [see Dosage and Administration (2.1) and Clinical Studies (14)].

Limitations of Use

VANFLYTA is not indicated as maintenance monotherapy following allogeneic hematopoietic stem cell transplantation (HSCT); improvement in overall survival with VANFLYTA in this setting has not been demonstrated [see Clinical Studies (14)].

2 DOSAGE AND ADMINISTRATION

2.1 Patient Selection

Select patients for the treatment of AML with VANFLYTA based on the presence of FLT3-ITD mutation positivity [see Clinical Studies (14)]. Information on FDA-approved tests for the detection of FLT3-ITD mutation in AML is available at: http://www.fda.gov/CompanionDiagnostics.

2.2 Recommended Dosage

- A treatment course consists of up to 2 cycles of VANFLYTA in combination with induction cytarabine and anthracycline, up to 4 cycles of VANFLYTA in combination with high-dose cytarabine consolidation, and up to 36 cycles of VANFLYTA as maintenance therapy [see Clinical Studies (14)] or until disease progression or unacceptable toxicity. VANFLYTA maintenance therapy should be initiated following consolidation chemotherapy upon blood count recovery of absolute neutrophil count >500/mm^3 and platelet count >50,000/mm^3.
- See Table 1 for the recommended dosage of VANFLYTA by phase of therapy.

Table 1: VANFLYTA Dosage Regimen
VANFLYTA Initiation | Induction [Patients can receive up to 2 cycles of induction.] | Consolidation [Patients can receive up to 4 cycles of consolidation.] | Maintenance
VANFLYTA Initiation | Starting on Day 8 (for 7 + 3 regimen) [For 5 + 2 regimen as the second induction cycle, VANFLYTA will be given on Days 6 to 19.] | Starting on Day 6 | Starting on Day 1
Dose | 35.4 mg orally once daily | 35.4 mg orally once daily | - Administer 26.5 mg orally once daily Days 1 through 14 of the first cycle if QTcF is less than or equal to 450 ms. - Increase the dose to 53 mg once daily on Day 15 of the first cycle if QTcF is less than or equal to 450 ms. Maintain the 26.5 mg once daily dose if QTcF greater than 500 ms was observed during induction or consolidation.
Duration (28-day cycles) | Two weeks in each cycle (Days 8 to 21) | Two weeks in each cycle (Days 6 to 19) | - Once daily with no break between cycles for up to 36 cycles

For patients who proceed to hematopoietic stem cell transplantation (HSCT), VANFLYTA should be stopped 7 days before the start of a conditioning regimen.

Administer VANFLYTA orally with or without food at approximately the same time each day. Swallow tablets whole. Do not cut, crush, or chew the tablets. If a dose of VANFLYTA is vomited, do not administer a replacement dose; wait until the next scheduled dose is due. If a dose of VANFLYTA is missed or not taken at the usual time, administer the dose as soon as possible on the same day and return to the usual schedule the following day. The patient should not take two doses on the same day.

2.3 Monitoring and Dosage Modifications for Adverse Reactions

Initiate VANFLYTA only if QTcF is less than or equal to 450 ms [see Warnings and Precautions (5.1)].

During induction and consolidation, perform ECGs prior to initiation and then once weekly during VANFLYTA treatment or more frequently as clinically indicated [see Warnings and Precautions (5.1)].

During maintenance, perform ECGs prior to initiation, once weekly for at least the first month following dose initiation and escalation, and thereafter as clinically indicated. Escalate the dose only if QTcF is less than or equal to 450 ms [see Dosage and Administration (2.2) and Warnings and Precautions (5.1)].

Correct electrolyte abnormalities (hypokalemia and hypomagnesemia), and if possible, avoid concomitant administration of drugs that prolong the QT interval [see Warnings and Precautions (5.1)].

For recommended dosage modifications due to adverse reactions, see Table 2. For dosage adjustments due to adverse reactions, see Table 3.

Table 2: Recommended Dosage Modifications for Adverse Reactions [see Warnings and Precautions (5.1) and Adverse Reactions (6.1)]
Adverse Reaction | Recommended Action
QTcF between 450 ms and 480 ms (Grade 1) | - Continue VANFLYTA dose.
QTcF between 481 ms and 500 ms (Grade 2) | - Reduce the dose of VANFLYTA (see Table 3) without interruption. - Resume VANFLYTA at the previous dose in the next cycle if QTcF has decreased to less than 450 ms. Monitor the patient closely for QT prolongation during the first cycle at the increased dose.
QTcF greater than 500 ms (Grade 3) | - Interrupt VANFLYTA. - Resume VANFLYTA at a reduced dose (see Table 3) when QTcF returns to less than 450 ms. - Maintain the 26.5 mg once daily dose during maintenance if QTcF greater than 500 ms was observed during induction or consolidation.
Recurrent QTcF greater than 500 ms (Grade 3) | - Permanently discontinue VANFLYTA if QTcF greater than 500 ms recurs despite appropriate dose reduction and correction/elimination of other risk factors (e.g., serum electrolyte abnormalities, concomitant QT prolonging medications).
Torsades de pointes, polymorphic ventricular tachycardia, signs/symptoms of life-threatening arrhythmia (Grade 4) | - Permanently discontinue VANFLYTA.
Grade 3 or 4 non-hematologic adverse reactions | - Interrupt VANFLYTA. - Resume treatment at the previous dose if adverse reaction improves to Grade 1 or less. - Resume treatment at a reduced dose (see Table 3) if adverse reaction improves to Grade 2. - Discontinue if Grade 3 or 4 adverse reaction persists beyond 28 days.
Grade 3 or 4 hypokalemia (<3 mmol/L) or hypomagnesemia (<0.4 mmol/L or <0.9 mg/dL) | - Interrupt VANFLYTA. - Correct hypokalemia and hypomagnesemia according to institutional guidelines. - VANFLYTA may be restarted at the previous dose when the adverse reaction improves to Grade 2 or less without symptoms.
Grade 4 neutropenia or thrombocytopenia after achieving remission [Recommend bone marrow evaluation.] | - Reduce VANFLYTA dose (see Table 3).
Grades are in accordance with National Cancer Institute Common Terminology Criteria for Adverse Events version 4.03 (NCI CTCAE v4.03).

Table 3: Recommended Dosage Adjustments for Adverse Reactions for VANFLYTA
Current Dosage | Modified Dosage
53 mg once daily | 35.4 mg once daily
35.4 mg once daily | 26.5 mg once daily
26.5 mg once daily | Interrupt
17.7 mg once daily | Interrupt

2.4 Dosage Modifications for Strong CYP3A Inhibitors

Reduce the dosage of VANFLYTA when used concomitantly with strong CYP3A inhibitors as shown in Table 4. If the current dosage is 17.7 mg once daily, interrupt VANFLYTA treatment for the duration of strong CYP3A inhibitor use. After discontinuation of a strong CYP3A inhibitor for 5 half-lives, resume the VANFLYTA dose that was taken before initiating the strong inhibitor [see Drug Interactions (7)].

Table 4: Dosage Adjustments for Concomitant Use with Strong CYP3A Inhibitors
Current Dosage | Modified Dosage
53 mg once daily | 26.5 mg once daily
35.4 mg once daily | 17.7 mg once daily
26.5 mg once daily | 17.7 mg once daily

3 DOSAGE FORMS AND STRENGTHS

Tablets:

- 17.7 mg quizartinib, white, round, film-coated, debossed with "DSC511"
- 26.5 mg quizartinib, yellow, round, film-coated, debossed with "DSC512"

4 CONTRAINDICATIONS

VANFLYTA is contraindicated in patients with severe hypokalemia, severe hypomagnesemia, long QT syndrome, or in patients with a history of ventricular arrhythmias or torsades de pointes [see Warnings and Precautions (5.1)].

5 WARNINGS AND PRECAUTIONS

5.1 QT Prolongation, Torsades de Pointes, and Cardiac Arrest

VANFLYTA prolongs the QT interval in a dose- and concentration-dependent manner. The mechanism of QTc interval prolongation is via inhibition of the slow delayed rectifier potassium current, IKs, as compared to all other medications that prolong the QTc interval, which is via the rapid delayed rectifier potassium current, IKr. Therefore, the level of QTc prolongation with VANFLYTA that predicts the risk of cardiac arrhythmias is unclear. Inhibition of IKs and IKr may leave patients with limited reserve leading to a higher risk of QT prolongation and serious cardiac arrhythmias, including fatal outcomes [see Clinical Pharmacology (12.2)]. Torsades de pointes, ventricular fibrillation, cardiac arrest, and sudden death have occurred in patients treated with VANFLYTA.

Of the 1,081 patients with AML treated with VANFLYTA in clinical trials, torsades de pointes occurred in approximately 0.2% of patients, cardiac arrest occurred in 0.6%, including 0.4% with a fatal outcome, and 0.1% of patients experienced ventricular fibrillation [see Adverse Reactions (6.1)]. These severe cardiac arrhythmias occurred predominantly during the induction phase.

Of the 265 patients with newly diagnosed FLT3-ITD-positive AML treated with VANFLYTA in combination with chemotherapy in the clinical trial, 2.3% were found to have a QTcF greater than 500 ms and 10% of patients had an increase from baseline QTcF greater than 60 ms. The clinical trial excluded patients with a QTcF ≥450 ms or other factors that increased the risk of QT prolongation or arrhythmic events (e.g., NYHA Class III or IV congestive heart failure, hypokalemia, family history of long QT interval syndrome). Therefore, avoid use in patients who are at significant risk of developing torsades de pointes, including uncontrolled or significant cardiac disease, recent myocardial infarction, heart failure, unstable angina, bradyarrhythmias, tachyarrhythmias, uncontrolled hypertension, high-degree atrioventricular block, severe aortic stenosis, or uncontrolled hypothyroidism.

Do not initiate treatment with VANFLYTA if the QTcF interval is greater than 450 ms. Do not use VANFLYTA in patients with severe hypokalemia, severe hypomagnesemia, long QT syndrome, or in patients with a history of ventricular arrhythmias or torsades de pointes [see Contraindications (4)].

Perform an ECG and correct electrolyte abnormalities prior to initiation of treatment with VANFLYTA. During induction and consolidation, perform an ECG prior to initiation and then once weekly during VANFLYTA treatment or more frequently as clinically indicated. During maintenance, perform ECGs prior to initiation, once weekly for at least the first month following dose initiation and escalation, and as clinically indicated thereafter. Do not escalate the dose if QTcF is greater than 450 ms [see Dosage and Administration (2.3)].

Perform ECG monitoring of the QT interval more frequently in patients who are at significant risk of developing QT interval prolongation and torsades de pointes, or following dose escalation.

Monitor and correct hypokalemia and hypomagnesemia prior to and during treatment with VANFLYTA. Maintain electrolytes in the normal range. Monitor electrolytes and ECGs more frequently in patients who experience diarrhea or vomiting.

Monitor patients more frequently with ECGs if coadministration of VANFLYTA with drugs known to prolong the QT interval is required [see Drug Interactions (7)].

Reduce the VANFLYTA dose when used concomitantly with strong CYP3A inhibitors, as they may increase quizartinib exposure [see Dosage and Administration (2.4)].

Reduce VANFLYTA if QTc increases to greater than 480 ms and less than 500 ms. Interrupt and reduce VANFLYTA if QTc increases to greater than 500 ms. Permanently discontinue VANFLYTA in patients who develop recurrent QTc greater than 500 ms or QTc interval prolongation with signs or symptoms of life-threatening arrhythmia [see Dosage and Administration (2.3)].

VANFLYTA is available only through a restricted program under a REMS [see Warnings and Precautions (5.2)].

5.2 VANFLYTA REMS

VANFLYTA is available only through a restricted distribution program under a REMS called the VANFLYTA REMS because of the serious risk of QT prolongation, torsades de pointes, and cardiac arrest [see Warnings and Precautions (5.1)].

Notable requirements of the VANFLYTA REMS include the following:

- Prescribers must be certified in the VANFLYTA REMS by enrolling and completing training.
- Prescribers must counsel patients receiving VANFLYTA about the risk of QT prolongation, torsades de pointes, and cardiac arrest, and provide patients with a Patient Wallet Card.
- Pharmacies that dispense VANFLYTA must be certified with the VANFLYTA REMS and must verify prescribers are certified through the VANFLYTA REMS.

Further information about the VANFLYTA REMS is available at www.VANFLYTAREMS.com or by telephone at 1-855-212-6670.

5.3 Embryo-Fetal Toxicity

Based on findings in animals and its mechanism of action, VANFLYTA can cause fetal harm when administered to a pregnant woman. In animal reproduction studies, administration of quizartinib to pregnant rats during organogenesis at exposures 3 times the maximum recommended human dose (MRHD) of 53 mg/day caused structural abnormalities and alterations to growth.

Advise pregnant women of the potential risk to a fetus. Advise females of reproductive potential to use effective contraception during treatment with VANFLYTA and for 7 months after the last dose. Advise males with female partners of reproductive potential to use effective contraception during treatment with VANFLYTA and for 4 months after the last dose [see Use in Specific Populations (8.1, 8.3)].

6 ADVERSE REACTIONS

The following clinically significant adverse reactions are described elsewhere in the labeling:

- QT Prolongation, Torsades de Pointes, and Cardiac Arrest [see Warnings and Precautions (5.1)]

6.1 Clinical Trials Experience

Because clinical trials are conducted under widely varying conditions, adverse reaction rates observed in the clinical trials of a drug cannot be directly compared to rates in the clinical trials of another drug and may not reflect the rates observed in practice.

Newly Diagnosed FLT3-ITD positive AML

The safety of VANFLYTA (35.4 mg orally once daily with chemotherapy, 26.5 mg to 53 mg orally once daily as maintenance) in adult patients with newly diagnosed FLT3-ITD positive AML is based on QuANTUM-First, a randomized, double-blind clinical trial of VANFLYTA (n=265) or placebo (n=268) with chemotherapy [see Clinical Studies (14)]. Among patients who received VANFLYTA, 38% were exposed for 6 months or longer and 30% were exposed for greater than one year. On the VANFLYTA plus chemotherapy arm, 65% and 44% of patients completed induction and consolidation therapy, respectively, compared to 65% and 34% of patients in the placebo plus chemotherapy arm.

Serious adverse reactions in ≥5% of patients who received VANFLYTA plus chemotherapy were: febrile neutropenia (11%). Fatal adverse reactions occurred in 10% of patients who received VANFLYTA plus chemotherapy, including sepsis (5%), fungal infections (0.8%), brain edema (0.8%), and one case each of febrile neutropenia, pneumonia, cerebral infarction, acute respiratory distress syndrome, pulmonary embolism, ventricular dysfunction, and cardiac arrest.

Permanent discontinuation due to an adverse reaction in patients in the VANFLYTA plus chemotherapy arm occurred in 20% of patients. The most frequent (≥2%) adverse reaction which resulted in permanent discontinuation in the VANFLYTA arm was sepsis (5%).

Dosage interruptions of VANFLYTA due to an adverse reaction occurred in 34% of patients. Adverse reactions which required dosage interruption in ≥2% of patients in the VANFLYTA arm included neutropenia (11%), thrombocytopenia (5%), and myelosuppression (3%).

Dose reductions of VANFLYTA due to an adverse reaction occurred in 19% of patients. Adverse reactions which required dosage reductions in ≥2% of patients in the VANFLYTA arm were neutropenia (9%), thrombocytopenia (5%), and electrocardiogram QT prolonged (4%).

The most common adverse reactions (≥10% with a difference between arms of ≥2% compared to placebo), including laboratory abnormalities, were lymphocytes decreased, potassium decreased, albumin decreased, phosphorus decreased, alkaline phosphatase increased, magnesium decreased, febrile neutropenia, diarrhea, mucositis, nausea, calcium decreased, abdominal pain, sepsis, neutropenia, headache, creatine phosphokinase increased, vomiting, upper respiratory tract infections, hypertransaminasemia, thrombocytopenia, decreased appetite, fungal infections, epistaxis, potassium increased, herpesvirus infections, insomnia, electrocardiogram QT prolonged, magnesium increased, sodium increased, dyspepsia, anemia, and eye irritation.

Tables 5 and 6 summarize adverse reactions and laboratory abnormalities observed in patients receiving VANFLYTA in the clinical trial.

Table 5: Adverse Reactions (≥10%) in Patients with Newly Diagnosed FLT3-ITD positive AML Who Received VANFLYTA (with a Difference Between Arms of ≥2% Compared to Placebo) in the Clinical Trial
Body System Adverse Reaction | VANFLYTA + Chemotherapy (N=265) |  | PLACEBO + Chemotherapy (N=268)
Body System Adverse Reaction | All Grades % | Grade 3 or 4 % | All Grades % | Grade 3 or 4 %
Blood and Lymphatic System Disorders
Febrile neutropenia [Including fatalities.] | 44 | 43 | 42 | 41
Neutropenia [Includes other related terms.] | 29 | 26 | 14 | 12
Thrombocytopenia | 18 | 13 | 13 | 12
Anemia | 11 | 6 | 7 | 5
Gastrointestinal Disorders
Diarrhea [Diarrhea includes colitis, diarrhea, enteritis, enterocolitis, gastroenteritis, and neutropenic colitis.] | 42 | 8 | 39 | 8
Mucositis [Mucositis includes anal inflammation, anal ulcer, anorectal discomfort, aphthous ulcer, laryngeal inflammation, laryngeal pain, mucosal inflammation, edema mucosal, esophageal pain, esophageal ulcer, esophagitis, oral blood blister, oral disorder, oral mucosa erosion, oral mucosal blistering, oral mucosal erythema, oral pain, oropharyngeal pain, pharyngeal inflammation, proctalgia, proctitis, stomatitis, tongue ulceration, and vaginal ulceration.] | 38 | 5 | 33 | 4.1
Nausea | 34 | 1.5 | 31 | 1.9
Abdominal pain | 30 | 2.3 | 22 | 1.1
Vomiting | 25 | 0 | 20 | 1.5
Dyspepsia | 11 | 0.4 | 9 | 0.7
Infections and Infestations
Sepsis [Sepsis includes acinetobacter infection, bacteremia, bacterial sepsis, corynebacterium bacteremia, device related bacteremia, device related sepsis, enterobacter sepsis, enterococcal bacteremia, enterococcal sepsis, escherichia bacteremia, escherichia sepsis, klebsiella bacteremia, klebsiella sepsis, neutropenic sepsis, pseudomonal bacteremia, pulmonary sepsis, sepsis, septic shock, staphylococcal bacteremia, staphylococcal infection, staphylococcal sepsis, stenotrophomonas sepsis, streptococcal sepsis, and streptococcal bacteremia.] , | 30 | 19 | 26 | 20
Upper respiratory tract infection | 21 | 2.6 | 12 | 3
Fungal infection [Fungal infection includes aspergillosis oral, aspergillus infection, bronchopulmonary aspergillosis, candida infection, candida sepsis, fungal infection, fungal sepsis, fungal skin infection, fusarium infection, gastrointestinal candidiasis, hepatic infection fungal, hepatosplenic candidiasis, lower respiratory tract infection fungal, mucormycosis, oral candidiasis, oral fungal infection, oropharyngeal candidiasis, systemic candida, systemic mycosis, tinea cruris, and vulvovaginal candidiasis.] , | 16 | 6 | 10 | 3
Herpesvirus infection [Herpesvirus infection includes disseminated varicella zoster virus infection, genital herpes, herpes simplex, herpesvirus infection, herpes zoster, oral herpes, and varicella zoster virus infection.] | 14 | 2.6 | 8 | 1.9
Nervous System Disorders
Headache | 28 | 0 | 20 | 0.7
Hepatobiliary disorders
Hypertransaminasemia [Hypertransaminasemia includes alanine aminotransferase increased, aspartate aminotransferase increased, transaminases increased, hepatic enzymes increased, and hypertransaminasemia.] | 19 | 7 | 14 | 6
Metabolism and Nutrition Disorders
Decreased appetite | 17 | 4.9 | 13 | 1.9
Respiratory, Thoracic and Mediastinal Disorders
Epistaxis | 15 | 1.1 | 11 | 0.4
Psychiatric Disorders
Insomnia | 14 | 0 | 11 | 0
Investigations
Electrocardiogram QT prolonged | 14 | 3 | 4.1 | 1.1
Eye Disorders
Eye irritation [Eye irritation includes dry eye, eye inflammation, eye irritation, eye pain, eye pruritus, foreign body sensation in eyes, keratitis, and ulcerative keratitis.] | 11 | 0 | 7 | 0

Laboratory Abnormalities

Prolonged thrombocytopenia or neutropenia in the absence of active leukemia lasting past cycle day 42 of induction cycle 1 were noted in 8% of patients on the VANFLYTA plus chemotherapy arm and 4% of patients in the placebo plus chemotherapy arm.

Table 6: Select Laboratory Abnormalities (≥10%) That Worsened from Baseline in Patients with Newly Diagnosed FLT3-ITD positive AML (with a Difference Between Arms of ≥2% Compared to Placebo) in the Clinical Trial
Laboratory Abnormality | VANFLYTA + Chemotherapy [The denominator used to calculate the rate varied from 199 to 260 in VANFLYTA + Chemotherapy and from 187 to 267 in PLACEBO + Chemotherapy based on the number of patients with a baseline value and at least one post-treatment value.] |  | PLACEBO + Chemotherapy
Laboratory Abnormality | All Grades% | Grades 3 or 4% | All Grades% | Grades 3 or 4%
Lymphocytes decreased | 60 | 57 | 55 | 51
Potassium decreased | 59 | 22 | 56 | 18
Albumin decreased | 53 | 1.6 | 45 | 4.3
Phosphorus decreased | 52 | 22 | 48 | 19
Alkaline phosphatase increased | 51 | 1.6 | 47 | 1.9
Magnesium decreased | 44 | 2 | 42 | 1.1
Calcium decreased | 33 | 2.4 | 27 | 1.6
Creatine phosphokinase increased | 26 | 2.5 | 7 | 0.5
Potassium increased | 15 | 1.2 | 11 | 0.8
Magnesium increased | 14 | 2.8 | 9 | 1.2
Sodium increased | 13 | 0 | 10 | 0.4

Other Clinical Trials

Clinically relevant adverse reactions in <10% of patients who received quizartinib for relapsed or refractory FLT3-ITD positive AML, an indication for which VANFLYTA is not approved, included differentiation syndrome (5%) and acute febrile neutrophilic dermatosis (3%).

7 DRUG INTERACTIONS

Table 7: Effect of Other Drugs on VANFLYTA
Strong CYP3A Inhibitors
Clinical Impact | VANFLYTA is a CYP3A substrate. Concomitant use of VANFLYTA with a strong CYP3A inhibitor increases quizartinib systemic exposure [see Clinical Pharmacology (12.3)], which may increase the risk of VANFLYTA adverse reactions.
Prevention or Management | Reduce the dosage of VANFLYTA [see Dosage and Administration (2.4)].
Strong or Moderate CYP3A Inducers
Clinical Impact | Concomitant use of VANFLYTA with strong or moderate CYP3A inducers decreases quizartinib systemic exposure [see Clinical Pharmacology (12.3)], which may reduce VANFLYTA efficacy.
Prevention or Management | Avoid concomitant use of VANFLYTA with strong or moderate CYP3A inducers [see Clinical Pharmacology (12.3)].
QT Interval Prolonging Drugs
Clinical Impact | VANFLYTA prolongs the QT/QTc interval. Coadministration of VANFLYTA with other drugs that prolong the QT interval may further increase the incidence of QT prolongation [see Warnings and Precautions (5.1) and Clinical Pharmacology (12.2)].
Prevention or Management | Monitor patients more frequently with ECG if coadministration of VANFLYTA with drugs known to prolong the QT interval is required. Examples of QT prolonging drugs include but are not limited to antifungal azoles, ondansetron, granisetron, azithromycin, pentamidine, doxycycline, moxifloxacin, atovaquone, prochlorperazine, and tacrolimus.

8 USE IN SPECIFIC POPULATIONS

8.1 Pregnancy

Risk Summary

Based on findings from animal studies and its mechanism of action, VANFLYTA can cause embryo-fetal harm when administered to a pregnant woman [see Clinical Pharmacology (12.1)].

There are no available data on VANFLYTA use in pregnant women to evaluate for a drug-associated risk. In animal reproduction studies, oral administration of quizartinib to pregnant rats during organogenesis resulted in adverse developmental outcomes including structural abnormalities and alterations to growth at maternal exposures approximately 3 times those in patients at the maximum recommended human dose (MRHD) of 53 mg/day (see Data). Advise pregnant women of the potential risk to a fetus.

The background risk in the U.S. general population of major birth defects is 2-4%, and of miscarriage is 15-20% of clinically recognized pregnancies.

Data

Animal Data

In an embryo-fetal development study in rats, pregnant animals received oral doses of quizartinib of 0, 0.6, 2, or 6 mg/kg/day during the period of organogenesis. Administration of quizartinib at the dose of 6 mg/kg/day was associated with adverse developmental outcomes including structural abnormalities (anasarca and edema) and alterations to growth (lower fetal weights and effects on skeletal ossification). At this dose, the maternal systemic exposures (AUC) were approximately 3 times the human exposure at the MRHD of 53 mg/day.

8.2 Lactation

Risk Summary

There are no data on the presence of quizartinib or its metabolites in human milk, or the effects on the breastfed child or milk production. Because of the potential for serious adverse reactions in a breastfed child, advise women not to breastfeed during treatment with VANFLYTA and for one month after the last dose.

8.3 Females and Males of Reproductive Potential

VANFLYTA can cause embryo-fetal harm when administered to pregnant women [see Use in Specific Populations (8.1)].

Pregnancy Testing

Verify pregnancy status in females of reproductive potential within seven days before starting treatment with VANFLYTA.

Contraception

Females

Advise female patients of reproductive potential to use effective contraception during treatment with VANFLYTA and for 7 months after the last dose.

Males

Based on genotoxicity findings, advise male patients with female partners of reproductive potential to use effective contraception during treatment with VANFLYTA and for 4 months after the last dose [see Nonclinical Toxicology (13.1)].

Infertility

Females

Based on findings from animal studies, VANFLYTA may impair female fertility. These effects on fertility were reversible [see Nonclinical Toxicology (13.1)].

Males

Based on findings from animal studies, VANFLYTA may impair male fertility. These effects on fertility were reversible [see Nonclinical Toxicology (13.1)].

8.4 Pediatric Use

Safety and effectiveness of VANFLYTA have not been established in pediatric patients.

8.5 Geriatric Use

There were 533 patients with newly diagnosed AML in the clinical study; of the total number of VANFLYTA-treated patients, 69 (26%) were 65 years of age and older, while 1 (0.4%) was 75 years of age [see Clinical Studies (14)]. No overall differences in safety or efficacy were observed between patients 65 years of age and older and younger adult patients.

8.6 Renal Impairment

No dosage adjustment is recommended in patients with mild to moderate renal impairment (i.e., estimated creatinine clearance [CLcr] by Cockcroft-Gault equation: CLcr 30 to 89 mL/min). VANFLYTA has not been studied in patients with severe renal impairment (CLcr <30 mL/min) [see Clinical Pharmacology (12.3)].

8.7 Hepatic Impairment

No dosage adjustment is recommended in patients with mild hepatic impairment (Child-Pugh Class A or total bilirubin ≤ upper limit of normal [ULN] and aspartate aminotransferase [AST] >ULN, or total bilirubin >1 to 1.5 times ULN and any value for AST) or moderate hepatic impairment (Child-Pugh Class B or total bilirubin >1.5 to 3 times ULN and any value for AST). VANFLYTA has not been studied in patients with severe (Child-Pugh Class C or total bilirubin >3 times ULN and any value for AST) hepatic impairment [see Clinical Pharmacology (12.3)].

11 DESCRIPTION

VANFLYTA (quizartinib) is a kinase inhibitor for oral use. The chemical name of quizartinib dihydrochloride is 1-(5-tert-butyl-1,2-oxazol-3-yl)-3-(4-{7-[2-(morpholin-4-yl)ethoxy]imidazo[2,1-b][1,3]benzothiazol-2-yl}phenyl)urea dihydrochloride. Quizartinib dihydrochloride is a white to off-white solid with a molecular formula of C29H32N6O4S∙2 HCl and a molecular weight of 633.6 for the salt and 560.7 for the free base. The aqueous solubility of quizartinib dihydrochloride (pKa 4.75 and 3.16) decreases with increasing pH. It is very slightly soluble in aqueous media at pH 1 and practically insoluble or insoluble at pH 2 and higher. Quizartinib dihydrochloride is very slightly soluble in ethanol. The chemical structure of quizartinib dihydrochloride is:

VANFLYTA is supplied as film-coated tablets containing 17.7 mg or 26.5 mg of quizartinib, which are equivalent to 20 mg and 30 mg quizartinib dihydrochloride, respectively. The inactive ingredients in the tablet core are hydroxypropyl betadex, microcrystalline cellulose, and magnesium stearate. The tablet coating consists of hypromellose, talc, triacetin, and titanium dioxide. The 26.5 mg tablet coating also contains ferric oxide.

12 CLINICAL PHARMACOLOGY

12.1 Mechanism of Action

Quizartinib is a small molecule inhibitor of the receptor tyrosine kinase FLT3. Quizartinib and its major active metabolite AC886 bind to the adenosine triphosphate (ATP) binding domain of FLT3 with comparable affinity, and both had 10-fold lower affinity towards FLT3-ITD mutation compared to FLT3 in a binding assay. Quizartinib and AC886 inhibited FLT3 kinase activity, preventing autophosphorylation of the receptor, thereby inhibiting downstream FLT3 receptor signaling and blocking FLT3-ITD-dependent cell proliferation. Quizartinib showed antitumor activity in a mouse model of FLT3-ITD-dependent leukemia.

12.2 Pharmacodynamics

The exposure-response relationship and time course of pharmacodynamic response for the safety and effectiveness of quizartinib have not been fully characterized.

Cardiac Electrophysiology

In vitro studies have shown that quizartinib is a predominant inhibitor of the slow delayed rectifier potassium current, IKs.

The exposure-response analysis predicted a concentration-dependent QTcF interval median prolongation of 18 and 24 ms [upper bound of 2-sided 90% confidence interval (CI): 21 and 27 ms] at the median steady-state Cmax of quizartinib at the 26.5 mg and 53 mg dose level during maintenance therapy [see Warnings and Precautions (5.1) and Drug Interactions (7)].

12.3 Pharmacokinetics

The pharmacokinetics of quizartinib and its major circulating active metabolite (AC886) were characterized in healthy subjects and in patients with cancer and are presented as geometric mean (percent coefficient of variation [%CV]) unless otherwise specified.

Steady state quizartinib concentrations were achieved at Day 15 following once daily dosage in patients with AML. Quizartinib exposure (AUC and Cmax) increased proportionally in the dose range of 26.5 mg (0.75 times the recommended 35.4 mg induction dose) to 79.5 mg (2.25 times the recommended 35.4 mg induction dose) in healthy subjects and 17.7 mg (0.5 times the recommended 35.4 mg induction dose) to 53 mg (1.5 times the recommended 35.4 mg induction dose) in patients with AML.

Table 8: Pharmacokinetic Properties of Quizartinib and AC886
 | Quizartinib | AC886
General Information
Steady state exposure following 35.4 mg VANFLYTA once daily during induction therapy in patients with newly diagnosed AML
Cmax | 140 ng/mL (71%) | 163 ng/mL (52%)
AUC0-24h | 2,680 ng∙h/mL (85%) | 3,590 ng∙h/mL (51%)
Steady state exposure following 35.4 mg VANFLYTA once daily during consolidation therapy in patients with newly diagnosed AML
Cmax | 204 ng/mL (64%) | 172 ng/mL (47%)
AUC0-24h | 3,930 ng∙h/mL (78%) | 3,800 ng∙h/mL (46%)
Steady state exposure following 53 mg VANFLYTA once daily during maintenance therapy in patients with newly diagnosed AML
Cmax | 529 ng/mL (60%) | 262 ng/mL (48%)
AUC0-24h | 10,200 ng∙h/mL (75%) | 5,790 ng∙h/mL (46%)
Accumulation ratio [Mean (±SD)] (AUC0-24h) | 5.4 (4.4) | 8.7 (6.8)

Absorption

The mean (SD) absolute bioavailability of quizartinib from the tablet formulation was 71% (±7%) in healthy subjects. After oral administration under fasted conditions, time to peak concentration (median Tmax) of quizartinib and AC886 measured post dose was approximately 4 hours (range 2 to 8 hours) and 5 to 6 hours (range 4 to 120 hours), respectively, in healthy subjects.

No clinically significant differences in the pharmacokinetics of quizartinib were observed when administered with a high-fat, high-calorie meal.

Distribution

Volume of distribution at steady state in healthy subjects was estimated to be 275 L (17%).

In vitro plasma protein binding of quizartinib and AC886 is 99% or greater.

In vitro blood-to-plasma ratio for quizartinib and AC886 ranges from 0.79-1.30 and 1.36-3.19, respectively.

Elimination

Total body clearance of quizartinib in healthy subjects was estimated to be 2.23 L/hour (29%).

The mean (SD) effective half-lives (t1/2) in patients with newly diagnosed AML for quizartinib and AC886 during maintenance therapy are 81 hours (±73) and 136 hours (±113), respectively.

Metabolism

In vitro quizartinib is primarily metabolized via oxidation by CYP3A4/5 and AC886 is formed and metabolized by CYP3A4/5.

Excretion

Following a single radiolabeled dose of quizartinib 53 mg to healthy subjects, 76.3% of the total radioactivity was recovered in feces (4% unchanged) and 1.64% in urine.

Specific Populations

There were no clinically significant differences in the exposure of quizartinib and AC886 based on age (range 18 to 91 years), sex, race (White 65%, Asian 18%, Black 9%), or body weight (range 37 to 153 kg).

Patients with Renal Impairment

Mild or moderate renal impairment (i.e., estimated creatinine clearance [CLcr] by Cockcroft-Gault equation: 30 to 89 mL/min) were not associated with clinically significant differences in the exposure of quizartinib and AC886.

The impact of severe renal impairment (CLcr <30 mL/min) on the pharmacokinetics of quizartinib and AC886 is unknown [see Use in Specific Populations (8.6)].

Patients with Hepatic Impairment

Mild (total bilirubin ≤ upper limit of normal [ULN] and aspartate aminotransferase [AST] >ULN or total bilirubin >1 to 1.5 times ULN and any value for AST) or moderate (total bilirubin >1.5 to 3 times ULN and any value for AST) hepatic impairment were not associated with clinically significant differences in the exposure of quizartinib and AC886.

The impact of severe hepatic impairment (Child-Pugh Class C or total bilirubin >3 times ULN and any value for AST) on the pharmacokinetics of quizartinib and AC886 is unknown [see Use in Specific Populations (8.7)].

Drug Interaction Studies and Model-Informed Approaches

Clinical Studies

Strong CYP3A Inhibitors

The AUC of quizartinib increased by 94% and the Cmax by 17% following coadministration of a single 53 mg quizartinib dose with ketoconazole (a strong CYP3A inhibitor). The AUCinf of AC886 decreased by 94% and Cmax by 60%.

Moderate CYP3A Inhibitors

A clinically significant change in quizartinib and AC886 exposure (Cmax and AUCinf) was not observed following coadministration of a single quizartinib dose with fluconazole (a moderate CYP3A inhibitor).

Strong or Moderate CYP3A Inducers

The AUCinf of quizartinib decreased by 90% and Cmax by 45% following concomitant use of a single 53 mg dose of quizartinib with efavirenz (a moderate CYP3A inducer). The AUC of AC886 decreased by 96% and the Cmax by 68%. The effect of concomitant use with a strong CYP3A inducer may result in even greater effect on quizartinib pharmacokinetics based on mechanistic understanding of the drugs involved.

Gastric Acid Reducing Agents

No clinically significant differences in quizartinib pharmacokinetics were observed when used concomitantly with lansoprazole (a proton pump inhibitor that reduces gastric acid).

Other Drugs

There were no clinically significant differences in the pharmacokinetics of P-gp substrates (dabigatran etexilate) or UGT1A1 substrates (raltegravir) when used concomitantly with quizartinib.

In Vitro Studies

Cytochrome P450 (CYP) Enzymes

Quizartinib does not inhibit CYP1A2, CYP2B6, CYP2C8, CYP2C9, CYP2C19, CYP2D6, or CYP3A4. Quizartinib does not induce CYP3A4, CYP1A2, or CYP2B6.

AC886 does not inhibit CYP1A2, CYP2B6, CYP2C8, CYP2C9, CYP2D6, CYP2C19, or CYP3A4. AC886 does not induce CYP3A4, CYP1A2, or CYP2B6.

Other Metabolic Pathways

Quizartinib inhibits UGT1A1.

Transporters

Quizartinib is a substrate for P-gp but not for BCRP, OATP1B1, OATP1B3, OCT1, OAT2, MATE1, or MRP2. AC886 is a substrate for BCRP but not for OATP1B1, OATP1B3, MATE1, or MRP2.

Quizartinib inhibits BCRP and inhibition of this transporter at the recommended dosage cannot be excluded.

13 NONCLINICAL TOXICOLOGY

13.1 Carcinogenesis, Mutagenesis, Impairment of Fertility

Carcinogenicity studies have not been conducted with quizartinib.

Quizartinib was mutagenic in a bacterial reverse mutation (Ames) assay and not mutagenic in an in vivo transgenic rat mutation assay. Quizartinib was not genotoxic in vitro in mouse lymphoma thymidine kinase mutation and human lymphocyte chromosome aberration assays, or in an in vivo rat bone marrow micronucleus assay.

Fertility studies in animals have not been conducted with quizartinib. However, adverse findings in male and female reproductive systems were observed in repeat-dose toxicity studies in rats and monkeys. Findings in female animals (rats or monkeys) included ovarian cysts, vaginal mucosal modifications, and atrophy of the uterus, ovary, and vagina, starting at exposures (AUC) approximately 0.2 times the MRHD of 53 mg/day. In male animals (rats and monkeys), findings included testicular seminiferous tubular degeneration, failure of sperm release, germ cell depletion in the testes, and oligospermia/aspermia, starting at exposures approximately 0.4 times the MRHD. After approximately one month of recovery period, all these findings except the vaginal mucosal modifications in the female rats were reversible.

14 CLINICAL STUDIES

The efficacy of VANFLYTA in combination with chemotherapy was evaluated in QuANTUM-First (NCT02668653), a randomized, double-blind, placebo-controlled study of 539 patients with newly diagnosed FLT3-ITD positive AML. FLT3-ITD status was determined prospectively with a clinical trial assay and verified retrospectively using the companion diagnostic LeukoStrat® CDx FLT3 Mutation Assay, which is an FDA-approved test for selection of patients with AML for VANFLYTA treatment.

Patients were stratified by age (<60 versus ≥60 years), white blood cell count at diagnosis (<40×10^9/L versus ≥40×10^9/L), and region (North America, Europe versus Asia, other regions). Patients were randomized (1:1) to receive VANFLYTA (n=268) or placebo (n=271) in combination with induction and consolidation therapy and as maintenance monotherapy according to the initial assignment, as follows: a) Induction: 35.4 mg orally once daily on Days 8-21 of 7 + 3 (cytarabine [100 or 200 mg/m^2/day] on Days 1 to 7 plus daunorubicin [60 mg/m^2/day] or idarubicin [12 mg/m^2/day] on Days 1 to 3) and on Days 8-21 or 6-19 of an optional second induction (7 + 3 or 5 + 2 [5 days cytarabine plus 2 days daunorubicin or idarubicin], respectively), b) Consolidation: 35.4 mg orally once daily on Days 6-19 of high-dose cytarabine (1.5 to 3 g/m^2 every 12 hours on Days 1, 3 and 5) for up to 4 cycles, and c) Maintenance: 26.5 mg orally once daily on Days 1 to 14 and 53 mg once daily thereafter for up to thirty-six 28-day cycles. There was no re-randomization at the start of post consolidation therapy. Patients who proceeded to hematopoietic stem cell transplantation (HSCT) initiated maintenance therapy after recovery from the HSCT.

The two treatment groups were generally balanced with respect to baseline demographics and disease characteristics. Of the 539 randomized patients, the median age was 56 years (range 20-75 years); 46% were male; 60% were White, 29% were Asian, 1% were Black, and 10% were other races. Eighty-four percent had an Eastern Cooperative Oncology Group (ECOG) baseline performance status of 0 or 1. The majority of the patients (72%) had intermediate risk cytogenetics at baseline. FLT3-ITD variant allelic frequency (VAF) was 3-25% in 36% of patients, >25-50% in 52% of patients, and >50% in 12% of patients. NPM1 mutations were identified in 52% of patients.

A second course of induction was administered to 20% of the patients, 65% initiated at least one cycle of consolidation, and 39% initiated maintenance. Among the patients who entered maintenance, 64% completed at least 12 cycles, 36% completed at least 24 cycles, and 16% completed all 36 planned cycles of maintenance. Twenty-nine percent (157/539) of the patients underwent HSCT in first complete remission (CR). The overall rate of HSCT (including the following settings: first CR, induction failure, or salvage after relapse) was 54% (144/268) in the VANFLYTA plus standard chemotherapy arm versus 47% (128/271) in the placebo plus standard chemotherapy arm. All patients were followed for survival.

Efficacy was established on the basis of overall survival (OS), measured from the date of randomization until death by any cause. The primary analysis was conducted after a minimum follow-up of 24 months after the randomization of the last patient. The study demonstrated a statistically significant improvement in OS for the VANFLYTA arm [hazard ratio (HR) 0.78; 95% CI: 0.62, 0.98; 2-sided p=0.0324] (see Figure 1).

Figure 1: Kaplan-Meier Curve for Overall Survival in QuANTUM-First

In an exploratory subgroup analysis of the 89/208 (43%) of patients who received maintenance therapy with VANFLYTA or placebo following consolidation chemotherapy, the OS HR was 0.40 (95% CI: 0.19, 0.84). Of 119/208 (57%) of patients who received maintenance therapy with VANFLYTA or placebo following HSCT, the OS HR was 1.62 (95% CI: 0.62, 4.22).

The CR rate in the VANFLYTA arm was 55% (95% CI: 48.7, 60.9) with a median duration of CR of 38.6 months (95% CI: 21.9, NE), and the CR rate in the placebo arm was 55% (95% CI: 49.2, 61.4) with a median duration of CR of 12.4 months (95% CI: 8.8, 22.7).

16 HOW SUPPLIED/STORAGE AND HANDLING

VANFLYTA (quizartinib) is supplied as round, film-coated tablets, packaged in bottles with a child-resistant closure.

STORAGE AND HANDLING

Store at 20°C to 25°C (68°F to 77°F); excursions permitted from 15°C to 30°C (59°F to 86°F) [See USP Controlled Room Temperature].

Tablet Strength | Tablet Description | Package Configuration | NDC
17.7 mg | White, round, film-coated, debossed with "DSC511", | 28-count bottle | 65597-504-28
17.7 mg | White, round, film-coated, debossed with "DSC511", | 14-count bottle | 65597-504-04
26.5 mg | Yellow, round, film-coated, debossed with "DSC512" | 28-count bottle | 65597-511-28
26.5 mg | Yellow, round, film-coated, debossed with "DSC512" | 14-count bottle | 65597-511-04

17 PATIENT COUNSELING INFORMATION

Advise the patient to read the FDA-approved patient labeling (Medication Guide).

QT Prolongation, Torsades de Pointes, and Cardiac Arrest

Inform patients of symptoms that may be associated with significant QTc interval prolongation including dizziness, lightheadedness, and fainting. Advise patients to report these symptoms and the use of all medications to their healthcare provider [see Warnings and Precautions (5.1)].

VANFLYTA REMS

VANFLYTA is available only through a restricted program called the VANFLYTA REMS. Inform patients that they will be given a VANFLYTA Patient Wallet Card that they should carry with them at all times and show to all of their healthcare providers. This card describes signs and symptoms related to QT prolongation/cardiac arrhythmia which, if experienced, should prompt the patient to immediately seek medical attention [see Warnings and Precautions (5.2)].

Drug Interactions

Advise patients to inform their healthcare providers of all concomitant medications, including over-the-counter medications, vitamins, and herbal products. Advise patients to avoid concomitant use of St. John's wort as it is a strong CYP3A inducer [see Drug Interactions (7)].

Embryo-Fetal Toxicity and Use of Contraceptives

Advise pregnant women of the potential risk to the fetus. Advise female patients of reproductive potential to use effective contraception during treatment with VANFLYTA and for 7 months after the last dose. Advise patients to notify their healthcare provider immediately in the event of a pregnancy or if pregnancy is suspected during VANFLYTA treatment. Advise male patients with female partners of reproductive potential to use effective contraception during treatment with VANFLYTA and for 4 months after the last dose [see Warnings and Precautions (5.3) and Use in Specific Populations (8.1, 8.3)].

Infertility

Advise females and males of reproductive potential that VANFLYTA may impair fertility [see Use in Specific Populations (8.3) and Nonclinical Toxicology (13.1)].

Lactation

Advise women not to breastfeed during treatment with VANFLYTA and for one month after the last dose [see Use in Specific Populations (8.2)].

Dosing and Storage Instructions

- Advise patients that VANFLYTA should be taken once daily at approximately the same time each day and may be taken with or without food.
- Advise patients to swallow tablets whole. Advise patients not to cut, crush, or chew the tablets [see Dosage and Administration (2.2)].
- Instruct patients that if a dose of VANFLYTA is vomited, not to take an additional dose that day, and to wait until the next scheduled dose on the following day. If a dose of VANFLYTA is missed or not taken at the usual time, instruct patients to take the dose as soon as possible on the same day and return to the usual dosing schedule the following day.
- Store VANFLYTA at room temperature from 20°C to 25°C (68°F to 77°F).

Manufactured for:
Daiichi Sankyo, Inc., Basking Ridge, NJ 07920

VANFLYTA® is a registered trademark of Daiichi Sankyo Company, Ltd.
Copyright © 2024, Daiichi Sankyo, Inc.

USPI-VAN-C2-0624-r002

MEDICATION GUIDE
VANFLYTA (van-FLITT-ah)
(quizartinib)
tablets

What is the most important information I should know about VANFLYTA?
VANFLYTA may cause serious side effects, including:

- Changes in the electrical activity of your heart called QT prolongation, torsades de pointes, and your heart stopping (cardiac arrest). QT prolongation can cause irregular heartbeats that can be life-threatening or lead to death. Your healthcare provider will check the electrical activity of your heart with a test called an electrocardiogram (ECG) and will also do blood tests to check your potassium and magnesium levels before and during treatment with VANFLYTA. Tell your healthcare provider right away if you have an irregular heartbeat or feel dizzy, lightheaded, or faint, or have diarrhea or vomiting.

VANFLYTA is available only through a restricted program called the VANFLYTA Risk Evaluation and Mitigation Strategy (REMS) due to the risk of QT prolongation, torsades de pointes, and cardiac arrest.
You will receive a VANFLYTA Patient Wallet Card from your healthcare provider. Carry the VANFLYTA Patient Wallet Card with you at all times and show it to all of your healthcare providers. The VANFLYTA Patient Wallet Card lists signs and symptoms of QT prolongation and torsades de pointes.
Get medical help right away if you develop any of the signs and symptoms listed on the VANFLYTA Patient Wallet Card. You may need to be treated in a hospital.
See "What are the possible side effects of VANFLYTA?" for more information about side effects.

What is VANFLYTA?
VANFLYTA is a prescription medicine used in combination with certain chemotherapy medicines and alone as maintenance therapy to treat adults with newly diagnosed acute myeloid leukemia (AML) with a FLT3-ITD mutation.
Your healthcare provider will perform a test to make sure that VANFLYTA is right for you.
VANFLYTA is not for use alone as maintenance therapy after a hematopoietic stem cell transplant.
It is not known if VANFLYTA is safe and effective in children.

Do not take VANFLYTA if you have very low potassium, very low magnesium, long QT syndrome, or a history of ventricular arrhythmias or torsades de pointes.

Before you take VANFLYTA, tell your healthcare provider about all of your medical conditions, including if you:

- have any heart problems.
- have low blood levels of potassium or magnesium.
- are pregnant or plan to become pregnant. VANFLYTA can harm your unborn baby. Tell your healthcare provider right away if you become pregnant or think you may be pregnant during treatment with VANFLYTA.
  - If you are able to become pregnant, your healthcare provider will perform a pregnancy test within 7 days before you start treatment with VANFLYTA.
  - Females who are able to become pregnant should use effective birth control (contraception) during treatment with VANFLYTA and for 7 months after the last dose of VANFLYTA.
  - Males who have female partners who are able to become pregnant should use effective birth control during treatment with VANFLYTA and for 4 months after the last dose of VANFLYTA.
  - Talk to your healthcare provider about birth control methods you can use during this time.
- are breastfeeding or plan to breastfeed. It is not known if VANFLYTA passes into your breast milk. Do not breastfeed during treatment with VANFLYTA and for 1 month after the last dose of VANFLYTA.

Tell your healthcare provider about all the medicines you take, including prescription and over-the-counter medicines, vitamins, and herbal supplements. VANFLYTA and other medicines may affect each other causing side effects.
Especially tell your healthcare provider if you take St. John's wort. You should not take St. John's wort during treatment with VANFLYTA.

How should I take VANFLYTA?

- Take VANFLYTA exactly as your healthcare provider tells you to. Do not change your dose or stop taking VANFLYTA unless your healthcare provider tells you to.
- Take VANFLYTA by mouth 1 time a day at about the same time each day.
- Take VANFLYTA with or without food.
- Swallow VANFLYTA tablets whole. Do not cut, crush, or chew the tablets.
- If you miss a dose of VANFLYTA or did not take it at your usual time, take your dose as soon as possible on the same day. Take your next dose at your usual time on the next day. Do not take 2 doses on the same day to make up for a missed dose.
- If you vomit after taking a dose of VANFLYTA, do not take another dose. Take your next dose at your usual time the next day.

What are the possible side effects of VANFLYTA?
VANFLYTA may cause serious side effects, including:

- See "What is the most important information I should know about VANFLYTA?"

The most common side effects of VANFLYTA include:

- low white blood cell counts
- changes in levels of electrolytes in the blood
- changes in liver function tests
- low white blood cell counts with fever
- diarrhea
- mouth sores
- nausea
- stomach (abdominal) pain
- serious infection throughout the body and organs (sepsis)
- headache
- vomiting

- upper respiratory tract infections
- low platelet counts
- decreased appetite
- fungal infections
- nosebleed
- herpesvirus infections
- trouble sleeping
- abnormal electrocardiogram (QT prolongation)
- upset stomach
- low red blood cell counts (anemia)
- eye irritation

Your healthcare provider will do blood tests and ECGs before you start and during treatment with VANFLYTA. Your healthcare provider may tell you to decrease your dose, temporarily stop, or permanently stop taking VANFLYTA if you develop certain side effects during treatment with VANFLYTA.
VANFLYTA may cause fertility problems in females and males, which may affect your ability to have children. Talk to your healthcare provider if you have concerns about fertility.
These are not all the possible side effects of VANFLYTA. Call your doctor for medical advice about side effects. You may report side effects to FDA at 1-800-FDA-1088.

How should I store VANFLYTA?

- Store VANFLYTA at room temperature between 68°F and 77°F (20°C and 25°C).

Keep VANFLYTA and all medicines out of the reach of children.

General information about the safe and effective use of VANFLYTA.
Medicines are sometimes prescribed for purposes other than those listed in a Medication Guide. Do not use VANFLYTA for a condition for which it is not prescribed. Do not give VANFLYTA to other people even if they have the same symptoms you have. It may harm them. You can ask your healthcare provider or pharmacist for information about VANFLYTA that is written for health professionals.

What are the ingredients in VANFLYTA?
Active ingredient: quizartinib
Inactive ingredients:

- Tablet core: hydroxypropyl betadex, microcrystalline cellulose, and magnesium stearate.
- Tablet coating: hypromellose, talc, triacetin, and titanium dioxide. The 26.5 mg tablet coating also contains ferric oxide.

Manufactured for: Daiichi Sankyo, Inc., Basking Ridge, NJ 07920
VANFLYTA® is a registered trademark of Daiichi Sankyo Company, Ltd.
Copyright © 2023, Daiichi Sankyo, Inc.
USMG-VAN-C1-0723-r001
For more information about VANFLYTA, ask your healthcare provider or pharmacist, visit http://www.vanflyta.com, or call 1-877-437-7763.

This Medication Guide has been approved by the U.S. Food and Drug Administration.

Issued: 7/2023

PRINCIPAL DISPLAY PANEL - 17.7 mg Tablet Bottle Carton

NDC 65597-504-04
14 tablets

VANFLYTA®
(quizartinib) tablets

17.7 mg

Rx only

Swallow tablets whole. Do not cut,
crush, or chew the tablets.

Dispense accompanying
Medication Guide to each patient.

Daiichi-Sankyo

PRINCIPAL DISPLAY PANEL - 26.5 mg Tablet Bottle Carton

NDC 65597-511-04
14 tablets

VANFLYTA®
(quizartinib) tablets

26.5 mg

Rx only

Swallow tablets whole. Do not cut,
crush, or chew the tablets.

Dispense accompanying
Medication Guide to each patient.

Daiichi-Sankyo